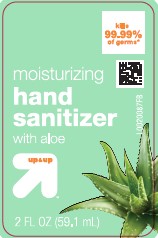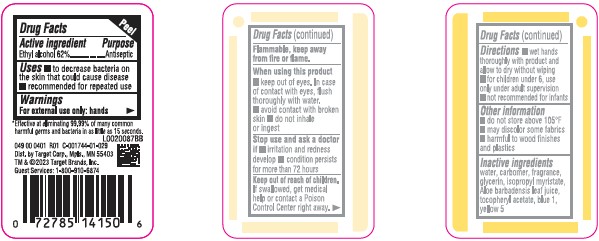 DRUG LABEL: Alcohol
NDC: 11673-826 | Form: LIQUID
Manufacturer: Target Corporation
Category: otc | Type: HUMAN OTC DRUG LABEL
Date: 20260218

ACTIVE INGREDIENTS: ALCOHOL 62 mL/100 mL
INACTIVE INGREDIENTS: CARBOMER INTERPOLYMER TYPE A (ALLYL SUCROSE CROSSLINKED); GLYCERIN; TOCOPHEROL; WATER; ISOPROPYL MYRISTATE; ALOE; FD&C BLUE NO. 1; FD&C YELLOW NO. 5

Up & Up 826.000/826AA rev 1
Moisturizing Hand Sanitizer with Aloe

Active ingredient

Ethyl Alcohol 62%

Purpose

Antiseptic

Uses

- to decrease bacteria on the skin that could cause disease
- recommended for repeated use

Warnings

For exterjnal use only: hands

Flammable, keep away from fire or flame

When using this product

- keep out of eyes. In case of contact with eyues, flush thoroughly with water.
- aoid contact with broken skin
- do not inhale of ingest

Stop use and ask a doctor if

- irritation and redness develop
- condition persists for more than 72 hours

Keep out of reach of children.

If swallowed, get medical help or contact a Poison Control Center right away.

Directions

- wet hands thoroughly with product and allow to dry without wiping
- for children under 6, use only under adult supervision
- not recommended for infants

Other information

- do not store above 105° F
- may discolor some fabrics
- harmful to wood finishes and plastics

Inactive ingredients

water, carbomer, fragrance, glycerin, isopropyl myristate, Aloe barbadensis leaf juice, tocopheryl acetate, blue 1, yellow 5

ADVERSE REACTION

*Effective at eliminating 99.99% of many common harmful germs and bacteria in as little as 15 seconds.

Dist. by Target Corp., Mpls., MN 55403

Made in U.S.A. with U.S. and foreign components

TM & ©2023 Target Brands, Inc.

Guest Servies: 1-800-910-6874

Principal display panel

kills 99.99% of germs*

moisturizing

hand sanitizer

with aloe

up & up™

2 FL OZ (59.1 mL)